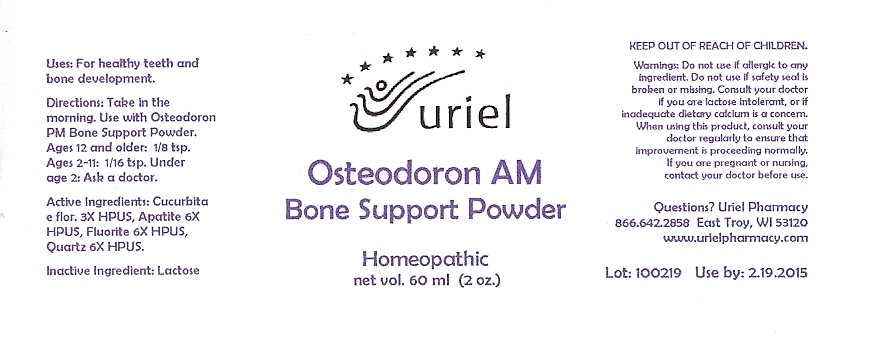 DRUG LABEL: Osteodoron AM Bone Support
NDC: 48951-7096 | Form: POWDER
Manufacturer: Uriel Pharmacy Inc
Category: homeopathic | Type: HUMAN OTC DRUG LABEL
Date: 20100312

ACTIVE INGREDIENTS: PUMPKIN 3 [hp_X]/1 1; SILICON DIOXIDE 6 [hp_X]/1 1; CALCIUM FLUORIDE 6 [hp_X]/1 1; FLUORAPATITE 6 [hp_X]/1 1
INACTIVE INGREDIENTS: LACTOSE

Osteodoron AM Bone Support Powder - 60 ml

Purpose

Uses: For healthy teeth and bone development.

Dosage & Administration

Directions: Take in the morning. Use with Osteodoron PM Bone Support Powder. Ages 12 and older: 1/8 tsp. Ages 2-11: 1/16 tsp. Under
age 2: Ask a doctor.

OTC-Active Ingredient

Active Ingredients: Cucurbita e flor. 3X HPUS, Apatite 6X HPUS, Fluorite 6X HPUS, Quartz 6X HPUS.

Inactive Ingredient

Inactive Ingredient: Lactose

Keep out of reach of children

Do not use section

Warnings:Do not use if allergic to any ingredient. Do not use if safety seal is broken or missing.

Ask doctor section

Consult your doctor if you are lactose intolerant, or if inadequate dietary calcium is a concern. When using this product, consult your doctor regularly to ensure that improvement is proceeding normally.

Pregnancy or breast feeding section

If you are pregnant or nursing, consult a doctor before use.

Questions section

Questions? Uriel Pharmacy
866.642.2858 East Troy, WI 53120
www.urielpharmacy.com

Principal Display Panel

Osteodoron AM

Bone Support Powder

Homeopathic

net vol. 60 ml (2 fl. oz.)